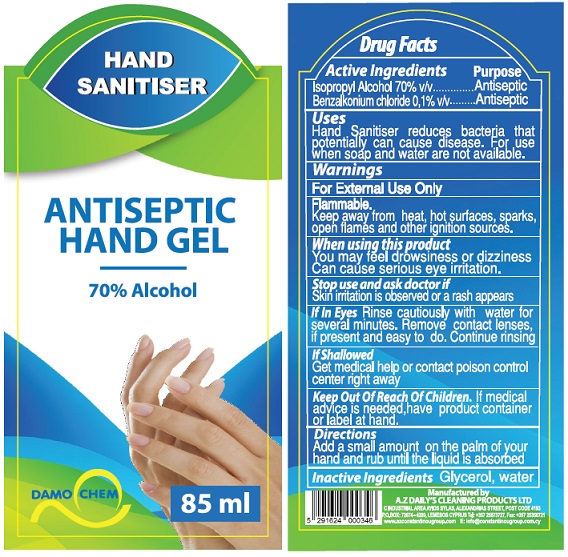 DRUG LABEL: Damochem Antiseptic Hand Gel
NDC: 77977-001 | Form: LIQUID
Manufacturer: A.Z Dailys Cleaning Products LTD
Category: otc | Type: HUMAN OTC DRUG LABEL
Date: 20200522

ACTIVE INGREDIENTS: ISOPROPYL ALCOHOL 70 mL/100 mL; BENZALKONIUM CHLORIDE 0.1 g/100 mL
INACTIVE INGREDIENTS: GLYCERIN; WATER

Active Ingredients

Alcohol 70% v/v.

Benzalkonium chloride 0.1% w/v

Purpose

Antiseptic

Uses

Hand Sanitizer to help reduce bacteria that potentially can cause disease. For use when soap and water are not available.

Warnings

For external use only.

Flammable. Keep away from heat, hot surfaces, caught sparks, open flames and other ignition sources.

When using this product
You may feel drowsiness or dizziness.
Can cause serious eye irritation.

Stop use and ask doctor if
skin irritation is observed or a rash appears

If in eyes, rinse cautiously with water for several minutes. Remove contact lenses, if present and easy to do. continue rinsing .

If swallowed, get medical help or contact a Poison Control Center right away.

Keep out of reach of children. If medical advice is needed, have product container or label at hand.

Directions

Add a small amount on palm of your hand and rub until the liquid is absorbed.

Inactive ingredients

Glycerol, Water